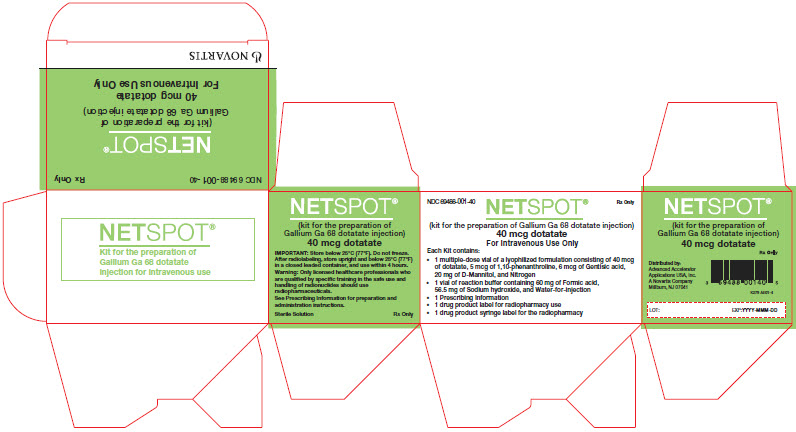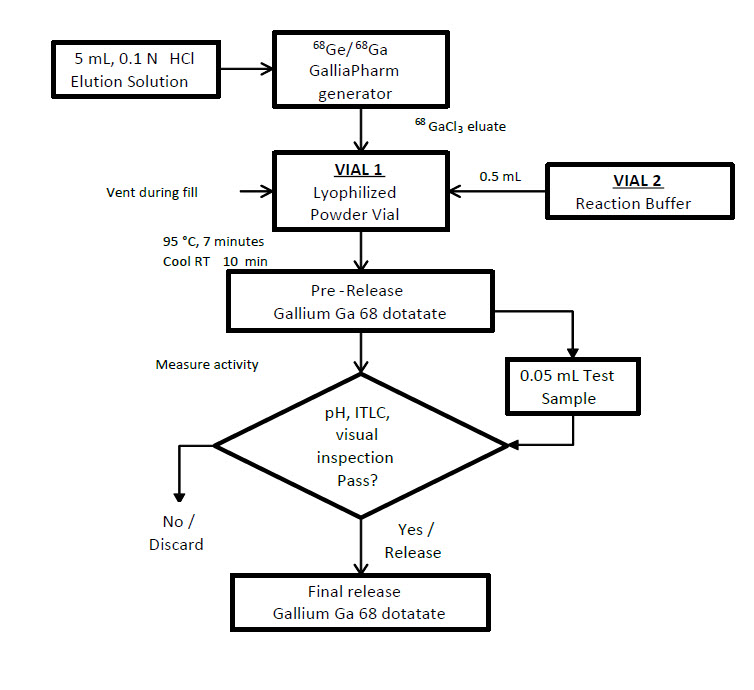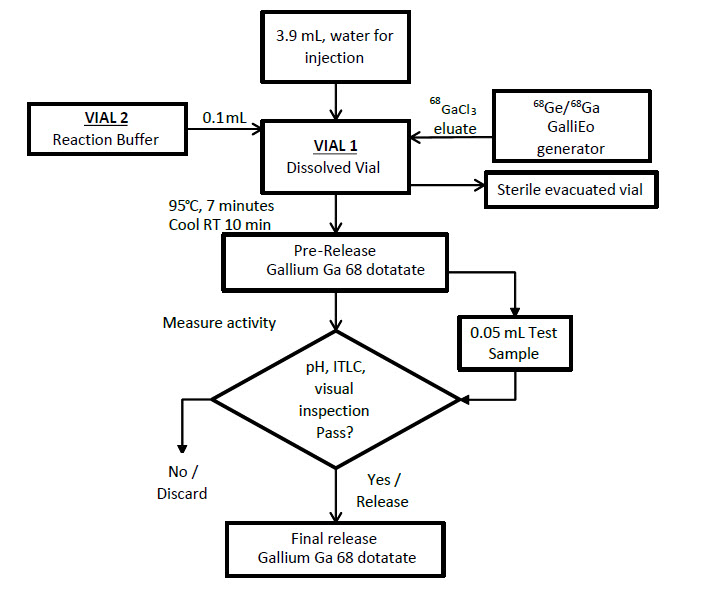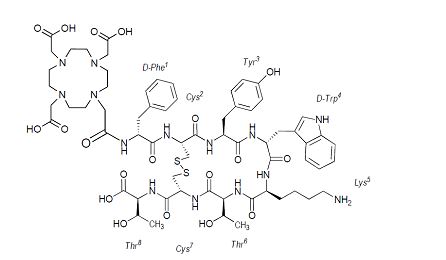 DRUG LABEL: NETSPOT
NDC: 69488-001 | Form: KIT | Route: INTRAVENOUS
Manufacturer: Advanced Accelerator Applications USA, Inc
Category: prescription | Type: HUMAN PRESCRIPTION DRUG LABEL
Date: 20260115

ACTIVE INGREDIENTS: DOTATATE 40 ug/1 1
INACTIVE INGREDIENTS: O-PHENANTHROLINE 5 ug/1 1; GENTISIC ACID 6 ug/1 1; MANNITOL 20 mg/1 1; FORMIC ACID 60 mg/1 1; SODIUM HYDROXIDE 56.5 mg/1 1; WATER

HIGHLIGHTS OF PRESCRIBING INFORMATION

These highlights do not include all the information needed to use NETSPOT safely and effectively. See full prescribing information for NETSPOT.
NETSPOT® (kit for the preparation of gallium Ga 68 dotatate injection), for intravenous use
Initial U.S. Approval: 2016

RECENT MAJOR CHANGES

Dosage and Administration (2.3) | 10/2023

1 INDICATIONS AND USAGE

NETSPOT, after radiolabeling with gallium-68, is a radioactive diagnostic agent indicated for use with positron emission tomography (PET) for localization of somatostatin receptor positive neuroendocrine tumors (NETs) in adult and pediatric patients. (1)

2 DOSAGE AND ADMINISTRATION

- After radiolabeling, handle gallium Ga 68 dotatate injection with appropriate safety measures to minimize radiation exposure. (2.1)
- Instruct patients to drink a sufficient amount of water before administration, during the first hours following administration and to void frequently. (2.1)
- Recommended dose is 2 MBq/kg (0.054 mCi/kg) of body weight up to 200 MBq (5.4 mCi) administered as intravenous bolus injection. (2.2)
- See the Full Prescribing Information for detailed instructions on how to prepare gallium Ga 68 dotatate injection (e.g., radiolabeling). (2.3)

3 DOSAGE FORMS AND STRENGTHS

NETSPOT is supplied as a multiple-dose kit containing:

- Vial 1 (reaction vial with lyophilized powder) containing 40 mcg of dotatate. (3)
- Vial 2 (buffer vial) containing 1 mL of reaction buffer solution. (3)

After radiolabeling with gallium-68 and pH adjustment with Reaction Buffer, Vial 1 contains a sterile solution of gallium Ga 68 dotatate at a strength up to 218 MBq/mL (5.89 mCi/mL). (3)

4 CONTRAINDICATIONS

None. (4)

5 WARNINGS AND PRECAUTIONS

- Radiation Risk: Gallium Ga 68 dotatate contributes to a patient’s overall long-term cumulative radiation exposure. Ensure safe handling and preparation procedures to protect patients and health care workers from unintentional radiation exposure. Restrict close contact with infants and pregnant women during the first 12 hours after administration of gallium Ga 68 dotatate. (5.1)
- Hypersensitivity Reactions: Most reported reactions were rash and pruritus and reversible either spontaneously or with routine symptomatic management. (5.2)
- Risk for Image Misinterpretation: The uptake of gallium Ga 68 dotatate can be seen in a variety of tumor types other than NETs (e.g., those derived from neural crest tissue), in sites of splenosis or other pathologic conditions, and as a normal physiologic variant (e.g., uncinate process of the pancreas). (5.3)

6 ADVERSE REACTIONS

Nausea, vomiting, and injection site pain and burning sensation were all reported during post-approval use. (6)

To report SUSPECTED ADVERSE REACTIONS, contact Novartis Pharmaceuticals Corporation at 1-888-669-6682 or FDA at 1-800-FDA-1088 or www.fda.gov/medwatch.

7 DRUG INTERACTIONS

Somatostatin Analogs: Somatostatin analogs competitively bind to the same somatostatin receptors as gallium Ga 68 dotatate and may affect imaging – image just prior to dosing with long-acting somatostatin analogs. (7.1)

Glucocorticoids: Repeated administration of high doses of glucocorticoids prior to gallium Ga 68 dotatate administration may affect imaging. (7.2)

8 USE IN SPECIFIC POPULATIONS

Lactation: Breast milk should be pumped and discarded for 12 hours after administration. (8.2)

FULL PRESCRIBING INFORMATION

1 INDICATIONS AND USAGE

NETSPOT, after radiolabeling with gallium-68, is indicated for use with positron emission tomography (PET) for localization of somatostatin receptor positive neuroendocrine tumors (NETs) in adult and pediatric patients.

2 DOSAGE AND ADMINISTRATION

2.1 Radiation Safety

Drug Handling
After radiolabeling, handle the gallium Ga 68 dotatate injection with appropriate safety measures to minimize radiation exposure [see Warnings and Precautions (5.1)]. Use waterproof gloves, effective radiation shielding and appropriate safety measures when preparing and handling gallium Ga 68 dotatate injection.

Radiopharmaceuticals should be used by or under the control of physicians who are qualified by specific training and experience in the safe use and handling of radionuclides, and whose experience and training have been approved by the appropriate governmental agency authorized to license the use of radionuclides.

Patient Preparation
Instruct patients to drink a sufficient amount of water to ensure adequate hydration prior to administration of gallium Ga 68 dotatate injection. Drink and void frequently during the first hours following administration to reduce radiation exposure.

2.2 Recommended Dosage and Administration Instructions

In adults and pediatric patients, the recommended amount of radioactivity to be administered for PET imaging is 2 MBq/kg (0.054 mCi/kg) of body weight up to 200 MBq (5.4 mCi) by intravenous injection (bolus).

Verify the injected radioactivity by measuring the radioactivity of the syringe containing the gallium Ga 68 dotatate injection with a dose calibrator before administration to the patient [see Dosage and Administration (2.4)]. Ensure that the injected radioactivity is within ± 10% of the recommended activity.

2.3 Drug Preparation

The NETSPOT kit is supplied as 2 vials [see Dosage Forms and Strengths (3)] which allows for direct preparation of gallium Ga 68 dotatate injection with the eluate from one of the following generators (see below for specific instructions for use with each generator):

- Eckert & Ziegler GalliaPharm germanium-68/gallium-68 (^68Ge/^68Ga) generator
- IRE ELiT Galli Eo germanium-68/gallium-68 (^68Ge/^68Ga) generator

The ^68Ge/^68Ga generators are not supplied with the NETSPOT kit.

Components of the kit:

- Vial 1 (reaction vial with lyophilized powder) contains: 40 mcg dotatate, 5 mcg 1,10-phenanthroline; 6 mcg gentisic acid; 20 mg mannitol.
- Vial 2 (buffer vial) contains: 60 mg formic acid; 56.5 mg sodium hydroxide and water for injection.

Ancillary supplies (not included in the kit):

- Ancillary supplies needed (not supplied in kit): 1 mL sterile plastic syringe, 5 mL sterile plastic syringe, non-metallic or silicone coated sterile needles (size 21 to 23G), 0.2 micron sterile vented filter.

Prepare gallium Ga 68 dotatate injection according to the following aseptic procedure:

a. Use suitable shielding to reduce radiation exposure.

b. Wear waterproof gloves.

c. Test periodically (weekly) the gallium-68 chloride eluate for germanium-68 breakthrough by suitable method. Germanium-68 breakthrough and other gamma emitting radionuclides should be ≤ 0.001%.

d. Set the temperature of the shielded dry bath to 95°C (203°F) and wait for the temperature to reach the set point and stabilize.

e. Prepare syringes for elution and radiolabeling steps per Table 1 below.

f. Use non-metallic or silicone coated needles to minimize trace metal impurity levels. Radiolabeling of carrier molecules with gallium-68 chloride is very sensitive to the presence of trace metal impurities.

g. Use 1 mL low dead space plastic syringe to precisely measure the adequate volume of reaction buffer to be added during preparation. Do not use glass syringe.

h. Prior to piercing vial septums, flip the cap off and swab the top of the vial closure with alcohol to disinfect the surface, and allow the stopper to dry.

Table 1. Solutions for Generator Elution and Radiolabeling Reaction
Solutions for use with Eckert & Ziegler GalliaPharm generator
Syringe | Solution | Purpose
5 mL sterile plastic syringe | 5 mL of 0.1 N sterile HCl supplied by the generator manufacturer | For elution of the generator
1 mL sterile plastic syringe | Vial 2 buffer; Calculate the volume (in mL) by multiplying the volume of HCl used for the elution of the generator in mL by its molarity:; Reaction buffer volume in mL = HCl volume in mL x HCl molarity (5 mL x 0.1 N = 0.5 mL of reaction buffer). | For radiolabeling reaction
Solutions for use with IRE Galli Eo generator
5 mL sterile plastic syringe | 3.9 mL sterile water for injection | For preliminary dilution of Vial 1
1 mL sterile plastic syringe | Vial 2 buffer; Calculate the volume (in mL) by multiplying the volume of HCl used for the elution of the generator in mL by its molarity:; Reaction buffer volume in mL = HCl volume in mL x HCl molarity (1.1 mL x 0.1 N = 0.11 mL of reaction buffer). | For radiolabeling reaction

i. Pierce the Vial 1 septum with a sterile needle connected to a 0.2 micron sterile vented filter (not supplied) to maintain atmospheric pressure within the vial during the radiolabeling process.

j. Follow the generator specific radiolabeling procedures below. Then continue with the incubation step k.

Radiolabeling with Eckert & Ziegler GalliaPharm generator

- Connect the male luer of the outlet line of the GalliaPharm generator to a sterile needle (size 21G to 23G).
- Connect Vial 1 directly to the outlet line of the GalliaPharm generator by pushing the needle through the rubber septum and place the vial in a lead shield container.
- Elute the generator directly into the Vial 1 according to the instructions for use of the GalliaPharm generator that are supplied by Eckert & Ziegler, in order to reconstitute the lyophilized powder with 5 mL of eluate. Perform the elution manually or by means of a pump.
- At the end of the elution, disconnect the generator from Vial 1 by removing the needle from the rubber septum, and immediately (do not delay buffer addition more than 10 min) add the kit reaction buffer in the 1 mL sterile syringe (size 21G to 23G; the amount of reaction buffer was determined in Table 1).
- Withdraw the syringe and the 0.2 micron sterile air venting filter.

Radiolabeling with IRE Galli Eo generator

- Set the Galli Eo generator for the elution according to manufacturer instructions. Connect a sterile needle (size 21G to 23G) to the outlet tube of the generator, turn the button by 90° to loading position then wait 10 seconds before turning the button back to the initial position.
- Reconstitute Vial 1 with 3.9 mL of sterile water for injection as prepared in Table 1.
- Add the 0.1 mL reaction buffer to Vial 1 as prepared in Table 1.
- Connect Vial 1 to the outlet line of the Galli Eo generator by pushing the needle through the rubber septum.
- Connect one end of the two male luer ends of a sterile extension line to the 0.2 micron sterile vent filter inserted into Vial 1.
- Assemble a sterile needle on the second male luer end of the sterile extension line and connect it to a sterile evacuated vial (17 mL minimum volume) by pushing the needle through the rubber septum. The generator elution will start.
- Wait for the elution to be completed (minimum 3 minutes, according to the Galli Eo generator manufacturer instructions for use).
- At the end of the elution, first withdraw the needle from the evacuated vial in order to establish atmospheric pressure into Vial 1, then disconnect Vial 1 from the generator by removing the needle from the rubber septum and remove the 0.2 micron sterile vent filter from Vial 1.

Incubation

k. Using a tong, move Vial 1 to the heating hole of the dry bath, and leave the vial at 95°C (203°F), not to exceed 98°C (208°F), for at least 7 minutes (do not exceed 10 minutes heating) without agitation or stirring.

l. After 7 minutes, remove the vial from the dry bath, place it in an appropriate lead shield and let it cool down to room temperature for approximately 10 minutes.

m. Assay the whole vial containing the gallium Ga 68 dotatate injection for total radioactivity concentration using a dose calibrator and record the result.

n. Perform the quality controls according to the recommended methods in order to check the compliance with the specifications [see Dosage and Administration (2.5)].

o. Prior to use, visually inspect the solution behind a shielded screen for radioprotection purposes. Only use solutions that are clear without visible particles.

p. Keep the vial containing the gallium Ga 68 dotatate injection upright in a radio-protective shield container at a temperature below 25°C (77°F) until use.

q. After addition of gallium-68 chloride to the reaction vial, use gallium Ga 68 dotatate injection within 4 hours. After radiolabeling, do not perform further dilutions.

Figure 1. Radiolabeling Procedure for Eckert & Ziegler GalliaPharm Generator

Figure 2. Radiolabeling Procedure for IRE Galli Eo Generator

2.4 Administration

Prior to use, visually inspect the prepared gallium Ga 68 dotatate injection behind a lead glass shield for radioprotection purposes. Only use solutions that are clear without visible particles. Using a single-dose syringe fitted with a sterile needle (size 21G to 23G) and protective shielding, aseptically withdraw the prepared gallium Ga 68 dotatate injection prior to administration. Measure the total radioactivity in the syringe by a dose calibrator immediately prior to administration. The dose calibrator must be calibrated with National Institute of Standards and Technology (NIST) traceable standards.

Accidental extravasation may cause local irritation due to the acidic pH of the gallium Ga 68 dotatate injection. In case of extravasation, the injection must be stopped, the site of injection must be changed and the affected area should be irrigated with 0.9% Sodium Chloride Injection, USP.

Handle and dispose radioactive material in accordance with applicable regulations.

2.5 Specifications and Quality Control

Perform the quality controls in Table 2 behind a lead glass shield for radioprotection purposes.

Table 2. Specifications of Gallium Ga 68 Dotatate Injection
Test | Acceptance criteria | Method
Appearance | Colorless and particulate free | Visual inspection
pH | 3.2 to 3.8 | pH-indicator strips
Labeling efficiency | Gallium Ga 68 dotatate ≥ 95% and other gallium-68 species ≤ 5% | Thin layer chromatography (ITLC, see details below)

Determine labeling efficiency of gallium Ga 68 dotatate injection applying one of the following recommended methods:

Obtain the following materials:

- ITLC SA or ITLC SG
- Ammonium acetate 1M: Methanol (1:1 V/V)
- Developing tank
- Radiometric TLC scanner

ITLC methods 1 and 2 (longer development length)

Perform the following:

1. Pour ammonium acetate 1M: Methanol (1:1 V/V) solution to a depth of 3 mm to 4 mm in the developing tank, cover the tank, and allow it to equilibrate.
2. Apply a drop of the gallium Ga 68 dotatate injection on a pencil line 1 cm from the bottom of the ITLC strip.
3. Place the ITLC strip in the developing tank and allow it to develop for a distance of 10 cm from the point of application (i.e., to the top pencil mark).
4. Scan the ITLC with a radiometric TLC scanner.
5. Calculate radiochemical purity (RCP) by integration of the peaks on the chromatogram. Do not use the reconstituted product if the RCP is less than 95%.
6. The retention factor (Rf) specifications are as follows for ITLC SA or ITLC SG:
  ITLC SA: Non-complexed gallium-68 species, Rf = 0 to 0.1; gallium Ga 68 dotatate, Rf = 0.6 to 0.8
  ITLC SG: Non-complexed gallium-68 species, Rf = 0 to 0.1; gallium Ga 68 dotatate, Rf = 0.8 to 1

ITLC method 3 (shorter development length)

Perform the following:

a) Pour ammonium acetate 1M: Methanol (1:1 V/V) solution to a depth of 3 mm to 4 mm in the developing tank, cover the tank, and allow it to equilibrate.

b) Apply a drop of the gallium Ga 68 dotatate injection on a pencil line 1 cm from the bottom of an ITLC SG strip.

c) Place the ITLC SG strip in the developing tank and allow it to develop for a distance of 6 cm from the point of application (i.e., to 7 cm from the bottom of the ITLC strip).

d) Scan the ITLC SG with a radiometric TLC scanner.

e) Calculate radiochemical purity (RCP) by integration of the peaks on the chromatogram. Do not use the reconstituted product if the RCP is less than 95%.

f) The retention factor (Rf) specifications are as follows:
Non-complexed gallium-68 species, Rf = 0 to 0.1; gallium Ga 68 dotatate, Rf = 0.8 to 1

2.6 Image Acquisition

For gallium Ga 68 dotatate PET imaging, the acquisition must include a whole body acquisition from skull to mid-thigh. Images can be acquired 40 minutes to 90 minutes after the intravenous administration of the gallium Ga 68 dotatate. Adapt imaging acquisition delay and duration according to the equipment used, and the patient and tumor characteristics, in order to obtain the best image quality possible.

2.7 Image Interpretation

Gallium Ga 68 dotatate binds to somatostatin receptors. Based upon the intensity of the signals, PET images obtained using gallium Ga 68 dotatate indicate the presence and density of somatostatin receptors in tissues. Tumors that do not bear somatostatin receptors will not be visualized. Increased uptake in tumors is not specific for NET [see Warnings and Precautions (5.3)].

2.8 Radiation Dosimetry

Estimated radiation absorbed doses per injection activity for organs and tissues of adult patients following an intravenous bolus of gallium Ga 68 dotatate are shown in Table 3. Estimated radiation effective doses per injection activity for adult and pediatric patients following an intravenous bolus of gallium Ga 68 dotatate are shown in Table 4.

Gallium-68 decays with a half-life of 68 minutes to stable zinc-68:

- 89% through positron emission with a mean energy of 836 keV followed by photonic annihilation radiations of 511 keV (178%),
- 10% through orbital electron capture (X-ray or Auger emissions), and
- 3% through 13 gamma transitions from 5 exited levels.

The radiation effective dose resulting from the administration of 150 MBq (4.05 mCi) [within the range of the recommended gallium Ga 68 dotatate injection dose] to an adult weighing 75 kg, is about 3.15 mSv. For an administered activity of 150 MBq (4.05 mCi) the typical radiation absorbed dose to the critical organs, which are the urinary bladder wall, the spleen, the kidneys and the adrenals, are about 15 mGy, 16 mGy, 14 mGy and 13 mGy, respectively. Because the spleen has one of the highest physiological uptakes, higher uptake and radiation dose to other organs or pathologic tissues may occur in patients with spleen disorders (e.g., splenectomy and/or splenosis) [see Warnings and Precautions (5.3)].

Physical data
Gamma constant: 0.67 mrem/hr per mCi at 1 meter [1.8E-4 mSv/hr per MBq at 1 meter]
Specific Activity: 4.1E7 Ci/g [1.51E18 Bq/g] max

Table 3. Estimated Radiation Absorbed Dose per Injection Activity in Selected Organs and Tissues of Adults from Intravenous Administration of Gallium Ga 68 Dotatate Injection
Organ/Tissue | Absorbed dose per administered activity (mGy/MBq)
 | Mean | SD
Adrenals | 0.086 | 0.052
Brain | 0.01 | 0.002
Breasts | 0.01 | 0.002
Gallbladder wall | 0.016 | 0.002
Lower large intestine wall | 0.015 | 0.002
Small intestine | 0.025 | 0.004
Stomach wall | 0.013 | 0.002
Upper large intestine wall | 0.021 | 0.003
Heart wall | 0.018 | 0.003
Kidneys | 0.093 | 0.016
Liver | 0.05 | 0.015
Lungs | 0.006 | 0.001
Muscle | 0.012 | 0.002
Ovaries | 0.016 | 0.001
Pancreas | 0.015 | 0.002
Red marrow | 0.015 | 0.003
Osteogenic cells | 0.021 | 0.005
Skin | 0.01 | 0.002
Spleen | 0.109 | 0.058
Testes | 0.01 | 0.001
Thymus | 0.012 | 0.002
Thyroid | 0.011 | 0.002
Urinary bladder wall | 0.098 | 0.048
Uterus | 0.015 | 0.002
Total body | 0.014 | 0.002
Effective dose per injection activity | mSv/MBq
 | 0.021 | 0.003

Table 4. Estimated Radiation Effective Dose per Injection Activity after a Gallium Ga 68 Dotatate Injection Dose
Age | Effective dose per injection activity (mSv/MBq)
Adult | 0.021
15 years | 0.025
10 years | 0.04
5 years | 0.064
1 year | 0.13
Newborn | 0.35

Table 4 indicates how effective dose per injection activity scales with body habitus in computational models of adult and pediatric patients.

3 DOSAGE FORMS AND STRENGTHS

NETSPOT is supplied as a multiple-dose kit, containing two vials for preparation of gallium Ga 68 dotatate injection:

- Vial 1 (reaction vial with lyophilized powder): 40 mcg of dotatate, 5 mcg of 1,10-phenanthroline, 6 mcg gentisic acid and 20 mg D-mannitol for injection as a white lyophilized powder in a 10 mL glass vial with light-blue flip-off cap
- Vial 2 (buffer vial): clear, and colorless reaction buffer solution (60 mg formic acid, 56.5 mg sodium hydroxide in approximately 1 mL volume) in a 10 mL olefin polymer vial with a yellow flip-off cap

Gallium-68 is obtained from one of the following generators:

- Eckert & Ziegler GalliaPharm (^68Ge/^68Ga) generator
- IRE ELiT Galli Eo (^68Ge/^68Ga) generator

After radiolabeling with gallium-68 and pH adjustment with Reaction Buffer, Vial 1 contains a sterile solution of gallium Ga 68 dotatate at a strength of up to 218 MBq/mL (5.89 mCi/mL).

4 CONTRAINDICATIONS

None.

5 WARNINGS AND PRECAUTIONS

5.1 Radiation Risk

Gallium Ga 68 dotatate contributes to a patient’s overall long-term cumulative radiation exposure. Long-term cumulative radiation exposure is associated with an increased risk of cancer. Ensure safe handling and preparation radiolabeling procedures to protect patients and health care workers from unintentional radiation exposure [see Dosage and Administration (2.1)].

Avoid close contact with infants and pregnant women during the first 12 hours after administration of gallium Ga 68 dotatate injection.

5.2 Hypersensitivity Reactions

Hypersensitivity reactions following administration of somatostatin receptor imaging agents predominantly consisted of cutaneous reactions, such as rash and pruritus. Reactions reversed either spontaneously or with routine symptomatic management. Less frequently hypersensitivity reactions included angioedema or cases with features of anaphylaxis.

5.3 Risk for Image Misinterpretation

The uptake of gallium Ga 68 dotatate reflects the level of somatostatin receptor density in NETs. However, uptake can also be seen in a variety of other tumor types (e.g., those derived from neural crest tissue). Increased uptake might also be seen in sites of splenosis or other pathologic conditions (e.g., thyroid disease or subacute inflammation) or might occur as a normal physiologic variant (e.g., uncinate process of the pancreas). PET images with gallium Ga 68 dotatate should be interpreted visually and the uptake may need to be confirmed by histopathology or other assessments [see Dosage and Administration (2.7)].

A negative scan after the administration of gallium Ga 68 dotatate in patients who do not have a history of NETs, including in patients suspected of ectopic ACTH-secreting tumors, does not rule out the presence of NETs.

6 ADVERSE REACTIONS

The following clinically significant adverse reactions are described elsewhere in the labeling:

- Hypersensitivity reactions [see Warnings and Precautions (5.2)]

6.1 Clinical Trials Experience

The safety of gallium Ga 68 dotatate was evaluated in three single center studies [see Clinical Studies (14)] and in a survey of the scientific literature. No serious adverse reactions were identified.

6.2 Postmarketing Experience

The following adverse reactions have been identified during post-approval use of NETSPOT or other somatostatin receptor imaging agents. Because these reactions are reported voluntarily from a population of uncertain size, it is not always possible to reliably estimate their frequency or establish a causal relationship to the drug.

Gastrointestinal Disorders: Nausea and vomiting

General Disorders and Administration Site Conditions: Injection site pain and burning sensation

Immune System Disorders: Hypersensitivity reactions, predominantly rash, pruritus, less frequently angioedema or features of anaphylaxis.

7 DRUG INTERACTIONS

7.1 Somatostatin analogs

Non-radioactive somatostatin analogs competitively bind to the same somatostatin receptors as gallium Ga 68 dotatate. Image patients with gallium Ga 68 dotatate PET just prior to dosing with long-acting analogs of somatostatin. Short-acting analogs of somatostatin can be used up to 24 hours before imaging with gallium Ga 68 dotatate.

7.2 Glucocorticoids

Glucocorticoids can down-regulate somatostatin subtype 2 receptors (SSTR2). Repeated administration of high doses of glucocorticoids prior to gallium Ga 68 dotatate administration may result in false negative imaging.

8 USE IN SPECIFIC POPULATIONS

8.1 Pregnancy

Risk Summary

There are no studies with gallium Ga 68 dotatate in pregnant women to inform any drug-associated risks; however, radioactive emissions, including those from gallium Ga 68 dotatate, can cause fetal harm. Animal reproduction studies have not been conducted with gallium Ga 68 dotatate.

In the U.S. general population, the estimated background risks of major birth defects and miscarriage in clinically recognized pregnancies are 2% to 4% and 15% to 20%, respectively.

8.2 Lactation

Risk Summary

There is no information on the presence of gallium Ga 68 dotatate in human milk, the effect on the breastfed child, or the effect on milk production. The developmental and health benefits of breastfeeding should be considered along with the mother’s clinical need for gallium Ga 68 dotatate injection and any potential adverse effects on the breastfed child from gallium Ga 68 dotatate injection or from the underlying maternal condition.

Clinical Considerations

Advise a lactating woman to interrupt breastfeeding and pump and discard breast milk for 12 hours after gallium Ga 68 dotatate administration in order to minimize radiation exposure to a breastfed child.

8.4 Pediatric Use

The efficacy of gallium Ga 68 dotatate PET imaging in pediatric patients with neuroendocrine tumors is based on extrapolation from adult studies, from studies demonstrating the ability of gallium Ga 68 dotatate to bind to somatostatin receptors [see Clinical Pharmacology (12.1)], and from a published study of gallium Ga 68 dotatate PET imaging in pediatric patients with somatostatin receptor positive tumors. The safety profile of gallium Ga 68 dotatate is similar in adult and pediatric patients with somatostatin receptor positive tumors. The recommended gallium Ga 68 dotatate injection dose in pediatric patients is weight based as in adults [see Dosage and Administration (2.2)].

8.5 Geriatric Use

Clinical studies of gallium Ga 68 dotatate injection did not include sufficient numbers of subjects aged 65 and over, to determine whether they respond differently from younger subjects. Other reported clinical experience has not identified differences in responses between the elderly and younger patients.

10 OVERDOSAGE

In the event of a radiation overdose, the absorbed dose to the patient should be reduced where possible by increasing the elimination of the radionuclide from the body by reinforced hydration and frequent bladder voiding. A diuretic might also be considered. If possible, an estimate of the radioactive dose given to the patient should be performed.

11 DESCRIPTION

NETSPOT is supplied as a sterile, multiple-dose kit for preparation of gallium Ga 68 dotatate injection for intravenous use.

Dotatate, also known as DOTA-0-Tyr3-Octreotate, is a cyclic 8 amino acid peptide with a covalently bound chelator (dota). The peptide has the amino acid sequence: H-D-Phe-Cys-Tyr-D-Trp-Lys-Thr-Cys-Thr-OH, and contains one disulfide bond. Dotatate has a molecular weight of 1435.6 Daltons and its chemical structure is shown in Figure 3.

Figure 3. Chemical Structure of Dotatate

[(4,7,10-Tricarboxymethyl-1,4,7,10-tetrazacyclododec-1-yl)acetyl]-(D)-Phenylalanyl-(L)Cysteinyl-(L)-Tyrosyl-(D)-Tryptophanyl-(L)-Lysyl-(L)-Threoninyl-(L)-Cysteinyl-(L)-Threonine-cyclic(2-7)disulfide

NETSPOT is a kit with the following components:

- Vial 1 (reaction vial with lyophilized powder) contains: 40 mcg dotatate, 5 mcg 1,10-phenanthroline; 6 mcg gentisic acid; 20 mg mannitol.
- Vial 2 (buffer vial) contains: 60 mg formic acid; 56.5 mg sodium hydroxide and water for injection.

After radiolabeling, [see Dosage and Administration (2.3)], gallium Ga 68 dotatate injection also contains hydrochloric acid as an excipient derived from the generator eluate. The prepared gallium Ga 68 dotatate injection for intravenous use, is a sterile, pyrogen free, clear, colorless, buffered solution, with a pH between 3.2 and 3.8. Table 5, Table 6, and Table 7 display the principal radiation emission data, radiation attenuation by lead shielding, and physical decay of gallium-68.

Table 5. Principal Radiation Emission Data (> 1%)
Radiation/Emission | % Disintegration | Mean energy (MeV)
beta+ | 88% | 0.8360
beta+ | 1.1% | 0.3526
gamma | 178% | 0.5110
gamma | 3% | 1.0770
X-ray | 2.8% | 0.0086
X-ray | 1.4% | 0.0086

Table 6. Radiation Attenuation of 511 keV Photons by Lead (Pb) Shielding
Shield thickness (Pb) mm | Coefficient of attenuation
6 | 0.5
12 | 0.25
17 | 0.1
34 | 0.01
51 | 0.001

Table 7. Physical Decay Chart for Gallium-68
Minutes | Fraction remaining
0 | 1.000
15 | 0.858
30 | 0.736
60 | 0.541
90 | 0.398
120 | 0.293
180 | 0.158
360 | 0.025

12 CLINICAL PHARMACOLOGY

12.1 Mechanism of Action

Gallium Ga 68 dotatate binds to somatostatin receptors, with highest affinity for subtype 2 receptors (SSTR2). It binds to cells that express somatostatin receptors, including malignant cells, which overexpress SSTR2. Gallium-68 is a β+ emitting radionuclide with an emission yield that allows PET imaging.

12.2 Pharmacodynamics

The relationship between gallium Ga 68 dotatate plasma concentrations and successful imaging was not explored in clinical trials.

12.3 Pharmacokinetics

Distribution

Gallium Ga 68 dotatate distributes to all SSTR2-expressing organs, such as pituitary, thyroid, spleen, adrenals, kidneys, pancreas, prostate, liver, and salivary glands. There is no uptake in the cerebral cortex or in the heart, and usually thymus and lung uptakes are low.

Elimination

A total of 12% of the injected dose is excreted in urine in the first four hours post-injection.

13 NONCLINICAL TOXICOLOGY

13.1 Carcinogenesis, Mutagenesis, Impairment of Fertility

No animal studies on fertility, embryology, mutagenic potential, or carcinogenic potential have been conducted with gallium Ga 68 dotatate. However, genotoxicity studies conducted with a very similar molecule (mixture lutetium Lu 175 dotatate/dotatate) show that these non-radioactive compounds do not induce mutation at the TK locus of L5178Y mouse lymphoma cells in vitro, nor reverse mutation in Salmonella Typhimurium, or Escherichia coli (both in the absence or presence of S9 metabolic activation).

14 CLINICAL STUDIES

The efficacy of NETSPOT was established in three open label single center studies (Study A-C).

In Study A, 97 adult patients (mean age 54; 41 men and 56 women) with known or suspected neuroendocrine tumors (NETs) were evaluated with gallium Ga 68 dotatate PET. The gallium Ga 68 dotatate images were read by two independent readers blinded to clinical information. The reads were compared to CT and/or MR images and to indium In 111 pentetreotide images obtained with Single Photon Emission Computed Tomography (SPECT) within previous 3 years. Among 78 patients in whom CT and/or MR images and indium In 111 pentetreotide images were available, gallium Ga 68 dotatate PET was in agreement with the CT and/or MR images in 74 patients. Out of 50 patients with NETs localized by CT and/or MR imaging, gallium Ga 68 dotatate was positive in 48 patients, including 13 patients in whom indium In 111 pentetreotide was negative. Gallium Ga 68 dotatate was negative in 26 out of 28 patients in whom CT and/or MR imaging was negative.

Study B was a published study which involved 104 patients (mean age 58; 52 men and 52 women) with suspected NETs due to clinical symptoms, elevated levels of tumor markers, or indeterminate tumors suggestive of NET. Diagnostic performance of gallium Ga 68 dotatate PET in localizing tumor sites was retrospectively assessed using a reference standard: histopathology (n = 49) or clinical follow up of up to 5-month duration (n = 55). Images were interpreted by consensus between two on-site readers who were not blinded to clinical information. NET sites were localized by reference standard in 36 patients (all by histopathology). Out of these, gallium Ga 68 dotatate was positive, correctly identifying an NET site, in 29 patients and was falsely negative in seven. In 68 patients with no NET identified by a reference standard, the images were negative in 61 and falsely positive in seven patients.

Study C was a published study which involved 63 patients (mean age 58; 34 men and 29 women) evaluated for NET recurrence using a reference standard as described for Study B. Gallium Ga 68 dotatate images were interpreted independently by two central readers blinded to clinical information. Reader 1 correctly localized NETs in 23 out of 29 reference standard-positive patients and reader 2 correctly localized NETs in 22 such patients. In 34 patients with no NET identified by a reference standard, reader 1 was correct in 29 patients and reader 2 in 32.

16 HOW SUPPLIED/STORAGE AND HANDLING

16.1 How Supplied

NETSPOT is supplied as a multiple-dose kit (NDC# 69488-001-40) for preparing multiple doses of gallium-68 radiolabeled dotatate injection.

The kit contains:

- Vial 1 (10-mL Ultra inert Type I Plus glass vial, light-blue flip-off cap): 40 mcg of dotatate, 5 mcg 1,10-phenanthroline, 6 mcg gentisic acid, 20 mg mannitol as lyophilized powder (NDC# 69488-001-04)
- Vial 2 (10-mL cyclic olefin polymer vial, with a yellow flip-off cap): reaction buffer solution (approximately 1 mL volume), 60 mg formic acid, 56.5 mg sodium hydroxide and water for injection (NDC# 69488-001-01)

The radionuclide is not part of the kit. Before radiolabeling with gallium-68, the contents of this kit are not radioactive.

Expiry date is indicated on the original outer packaging, and on the vials. This medicinal product must not be used beyond the date indicated on the packaging.

16.2 Storage and Handling

For prolonged storage, store NETSPOT in its original packaging at room temperature below 25°C (77°F) (do not freeze). After radiolabeling [see Dosage and Administration (2.3)] with activities of up to 1,110 MBq (30 mCi), keep gallium Ga 68 dotatate injection upright with an appropriate shielding to protect from radiation, at a temperature below 25°C (77°F) (do not freeze), and use within 4 hours. The storage of the radiolabeled product must comply with regulatory requirements for radioactive materials.

17 PATIENT COUNSELING INFORMATION

Adequate Hydration

Advise patients to drink a sufficient amount of water to ensure adequate hydration before their PET study and urge them to drink and urinate as often as possible during the first hours following the administration of gallium Ga 68 dotatate injection, in order to reduce radiation exposure [see Dosage and Administration (2.3)].

Lactation

Advise a lactating woman to interrupt breastfeeding and pump and discard breast milk for 12 hours after gallium Ga 68 dotatate injection administration in order to minimize radiation exposure to a breastfed infant [see Use in Specific Populations (8.2)].

Close Contact

Advise patients to avoid close contact with infants and pregnant women during the first 12 hours after administration of gallium Ga 68 dotatate.

Distributed by:
Advanced Accelerator Applications USA, Inc. Millburn, NJ 07041
©2023 Advanced Accelerator Applications USA, Inc.
NETSPOT® is a registered trademark of Novartis AG and/or its affiliates.

T2023-68

PRINCIPAL DISPLAY PANEL

NDC 69488-001-40

Rx Only

NETSPOT®

(kit for the preparation of
Gallium Ga 68 dotatate injection)

40 mcg dotatate

For Intravenous Use Only

NOVARTIS